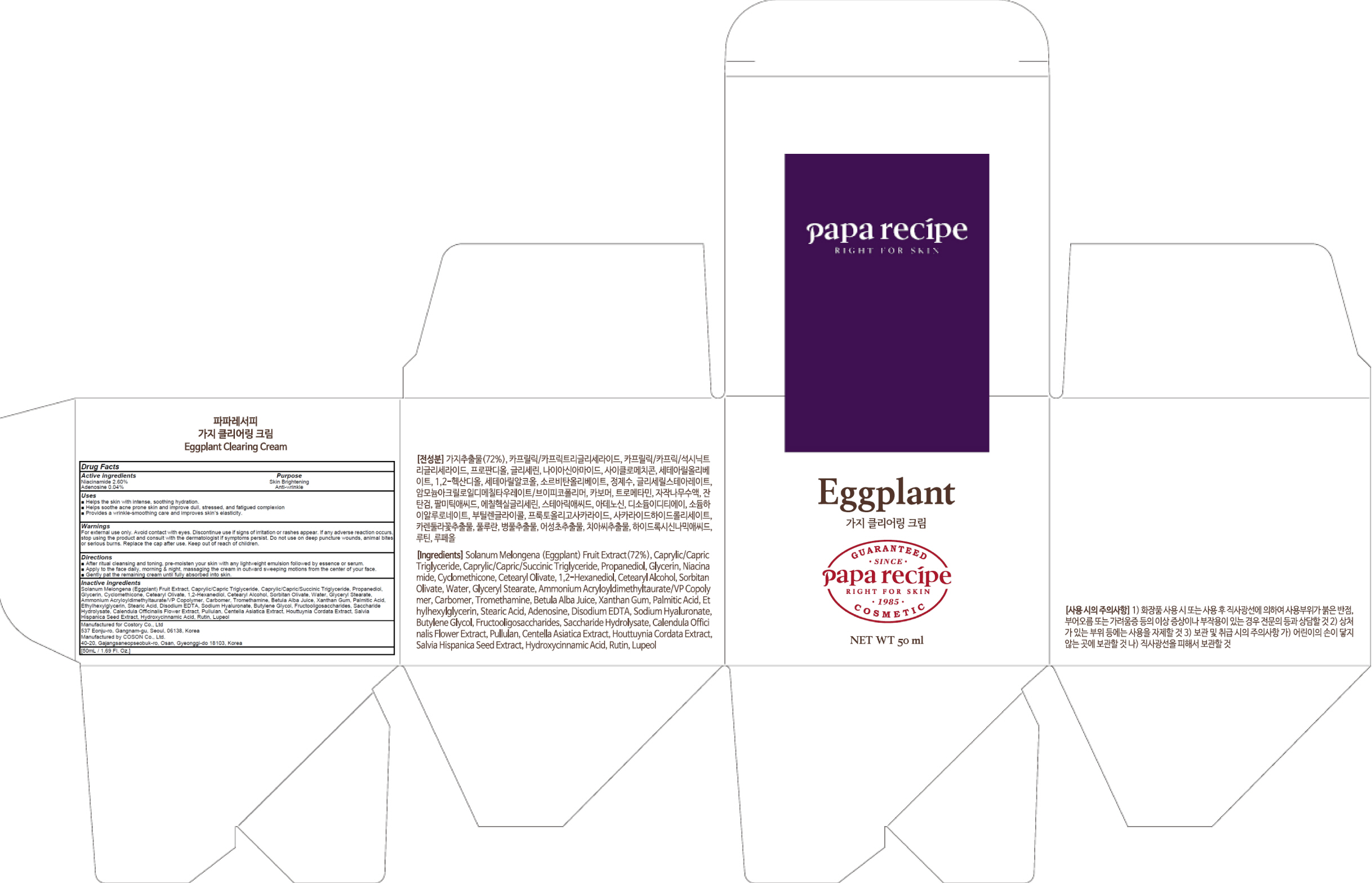 DRUG LABEL: PAPA RECIPE EGGPLANT CLEARING
NDC: 73020-060 | Form: CREAM
Manufacturer: Costory Co., Ltd
Category: otc | Type: HUMAN OTC DRUG LABEL
Date: 20190509

ACTIVE INGREDIENTS: Niacinamide 1.30 g/50 mL; Adenosine 0.02 g/50 mL
INACTIVE INGREDIENTS: Propanediol; Glycerin

ACTIVE INGREDIENT

Active ingredients: Niacinamide 2.60%, Adenosine 0.04%

INACTIVE INGREDIENT

Inactive ingredients:

Solanum Melongena (Eggplant) Fruit Extract, Caprylic/Capric Triglyceride, Caprylic/Capric/Succinic Triglyceride, Propanediol, Glycerin, Cyclomethicone, Cetearyl Olivate, 1,2-Hexanediol, Cetearyl Alcohol, Sorbitan Olivate, Water, Glyceryl Stearate, Ammonium Acryloyldimethyltaurate/VP Copolymer, Carbomer, Tromethamine, Betula Alba Juice, Xanthan Gum, Palmitic Acid,
Ethylhexylglycerin, Stearic Acid, Disodium EDTA, Sodium Hyaluronate, Butylene Glycol, Fructooligosaccharides, Saccharide Hydrolysate, Calendula Officinalis Flower Extract, Pullulan, Centella Asiatica Extract, Houttuynia Cordata Extract, Salvia Hispanica Seed Extract, Hydroxycinnamic Acid, Rutin, Lupeol

PURPOSE

Purpose: Skin Brightening, Anti-wrinkle

WARNINGS

For external use only. Avoid contact with eyes. Discontinue use if signs of irritation or rashes appear. If any adverse reaction occurs, stop using the product and consult with the dermatologist if symptoms persist. Do not use on deep puncture wounds, animal bites or serious burns. Replace the cap after use. Keep out of reach of children.

KEEP OUT OF REACH OF CHILDREN

Uses

■ Helps the skin with intense, soothing hydration.
■ Helps soothe acne prone skin and improve dull, stressed, and fatigued complexion
■ Provides a wrinkle-smoothing care and improve skin’s elasticity.

Directions

■ After ritual cleansing and toning, pre-moisten your skin with any lightweight emulsion followed by essence or serum.
■ Apply to the face daily, morning & night, massaging the cream in outward sweeping motions from the center of your face.
■ Gently pat the remaining cream until fully absorbed into skin.